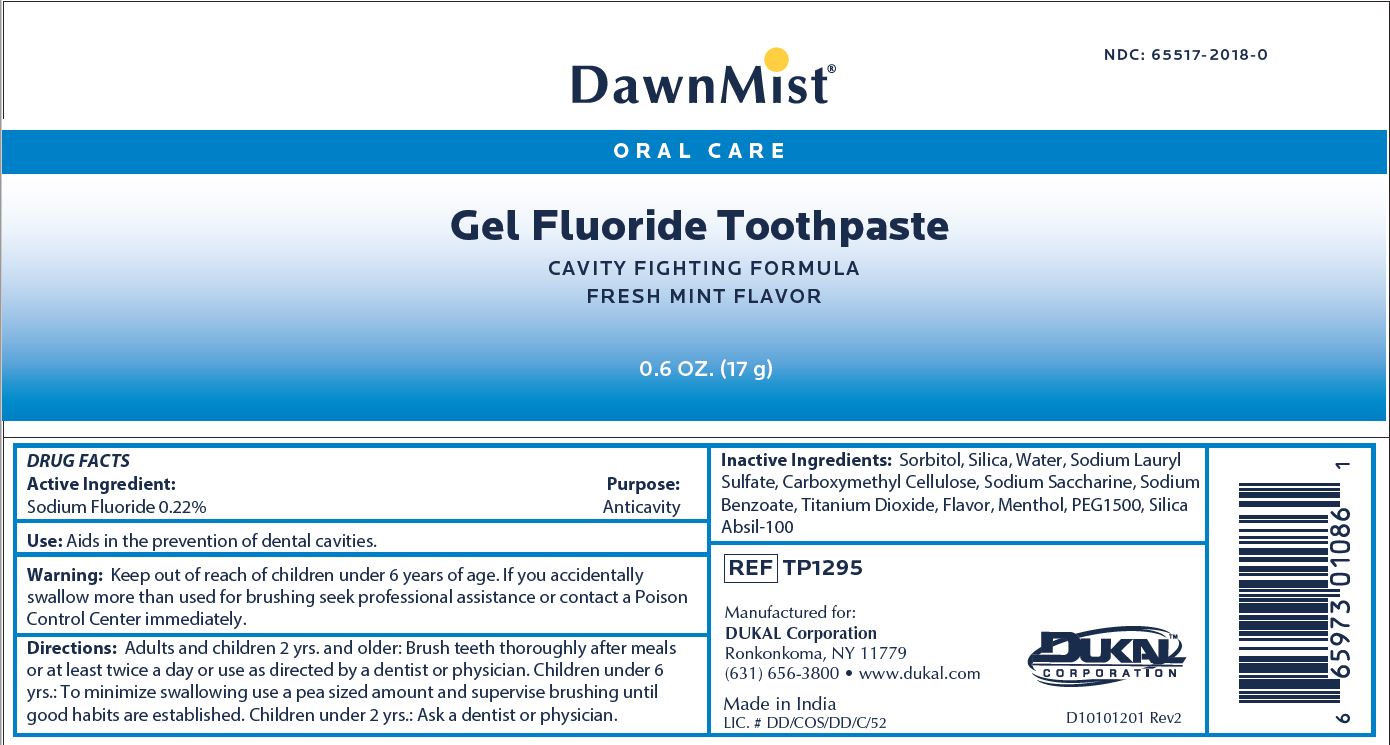 DRUG LABEL: DawnMist Fluoride
NDC: 65517-2018 | Form: PASTE
Manufacturer: Dukal LLC
Category: otc | Type: HUMAN OTC DRUG LABEL
Date: 20240708

ACTIVE INGREDIENTS: SODIUM FLUORIDE 0.76 g/100 g
INACTIVE INGREDIENTS: PEPPERMINT OIL; SORBITOL; SILICON DIOXIDE; WATER; SODIUM LAURYL SULFATE; POLYETHYLENE GLYCOL 1500; CARBOXYMETHYLCELLULOSE; SODIUM BENZOATE; SACCHARIN SODIUM; TITANIUM DIOXIDE

DawnMist Fluoride Toothpaste

Active Ingredient

Sodium Monofluorophosphate 0.76%

Purpose

Anticavity

Use

Aids in the prevention of dental cavities.

Warning:

Keep out of reach of children under 6 years of age.

If you accidentally swallow more than used for brushing seek professional assistance or contact a Poison Control Center immediately.

Directions

Adults and children 2 years and older: Brush teeth thoroughly after meals or at least twice a day or use as directed by a dentist or physician.

Children under 6 years: To minimize swallowing, use a pea sized amount and supervise brushing until good habits are established.

Children under 2 years: Ask a dentist or physician.

Inactive Ingredients

Sorbitol, Silica, Water, Sodium Lauryl Sulfate, Xanthan Gum, Sodium Benzoate, Titanium Dioxide, Mentha Piperita (Peppermint Oil), Sodium Saccharin

DawnMist Fluoride Toothpaste 0.6oz/17g (65517-2018-0)

DawnMist™ NDC: 65517-2018-0

ORAL CARE

Gel Fluoride Toothpaste

CAVITY FIGHTING FORMULA

FRESH MINT FLAVOR

0.6 OZ. (17g)